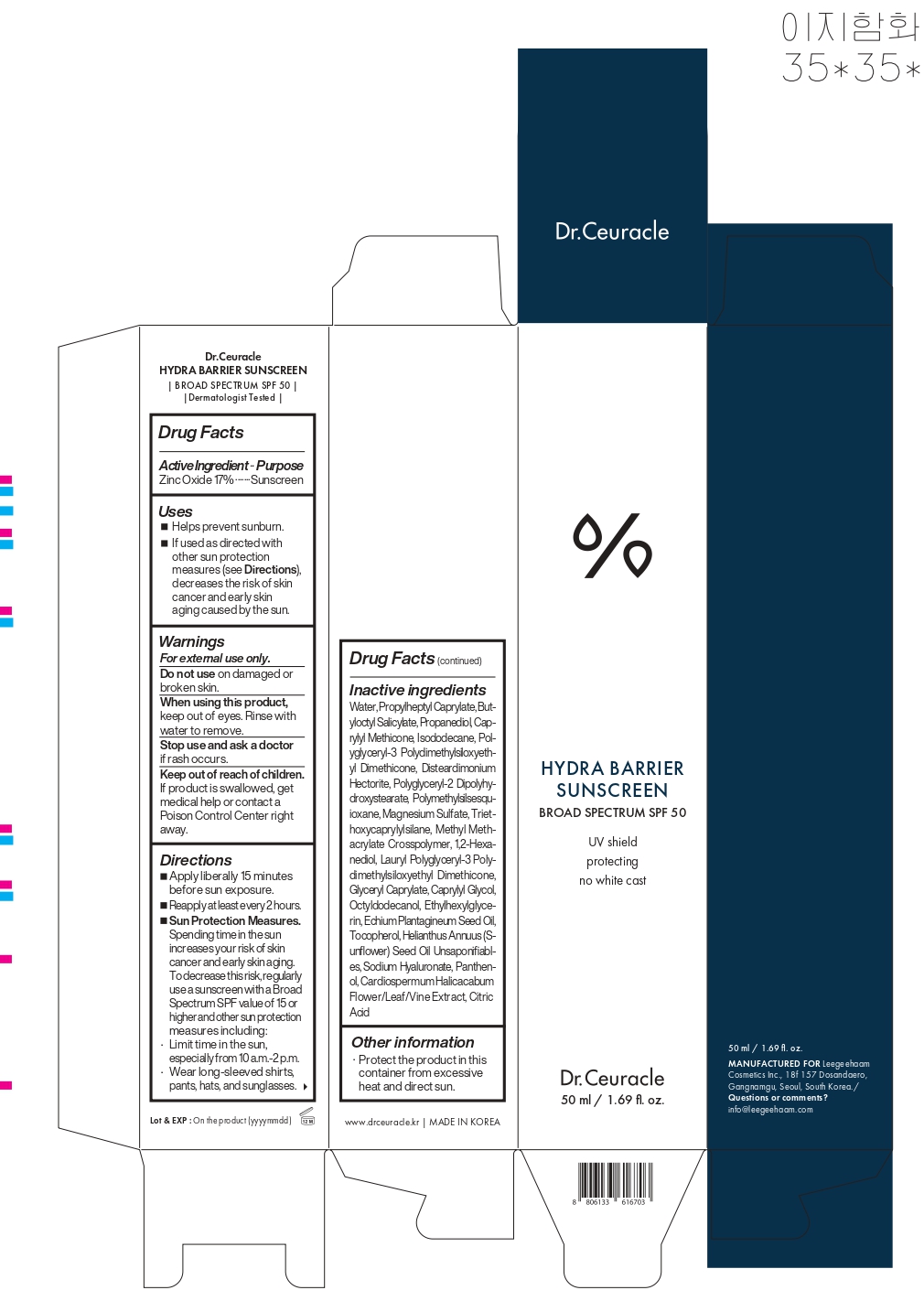 DRUG LABEL: Dr.Ceuracle HYDRA BARRIER SUNSCREEN
NDC: 84773-001 | Form: LOTION
Manufacturer: Leegeehaam Cosmetics
Category: otc | Type: HUMAN OTC DRUG LABEL
Date: 20250413

ACTIVE INGREDIENTS: ZINC OXIDE 170 mg/1 mL
INACTIVE INGREDIENTS: LAURYL POLYGLYCERYL-3 POLYDIMETHYLSILOXYETHYL DIMETHICONE (4000 MPA.S); ECHIUM PLANTAGINEUM SEED OIL; CARDIOSPERMUM HALICACABUM FLOWERING TOP; HYALURONATE SODIUM; WATER; BUTYLOCTYL SALICYLATE; POLYMETHYLSILSESQUIOXANE (4.5 MICRONS); CAPRYLYL GLYCOL; OCTYLDODECANOL; ETHYLHEXYLGLYCERIN; TOCOPHEROL; SUNFLOWER OIL UNSAPONIFIABLES; PANTHENOL; METHYL METHACRYLATE/GLYCOL DIMETHACRYLATE CROSSPOLYMER; TRIETHOXYCAPRYLYLSILANE; POLYGLYCERYL-2 DIPOLYHYDROXYSTEARATE; PROPANEDIOL; PROPYLHEPTYL CAPRYLATE; CAPRYLYL TRISILOXANE; POLYGLYCERYL-3 POLYDIMETHYLSILOXYETHYL DIMETHICONE (4000 MPA.S); MAGNESIUM SULFATE, UNSPECIFIED; 1,2-HEXANEDIOL; ISODODECANE; CITRIC ACID MONOHYDRATE; GLYCERYL CAPRYLATE; DISTEARDIMONIUM HECTORITE

Active Ingredient...Purpose

Zinc Oxide 17% ....... Sunscreen

Uses

Helps prevent sunburn.

If used as directed with other sun protection measures (see Directions), decreases the risk of skin cancer and early skin aging caused by the sun.

Warnings

For external use only.

Do not use on damaged or broken skin.

When using this product, keep out of eyes. Rinse with water to remove.

Stop use and ask a doctor if rash occurs.

Keep out of reach of children.
If product is swallowed, get medical help or contact a Poison Control Center right away.

Directions

- Apply liberally 15 minutes before sun exposure.
- Reapply at least every 2 hours.
- Sun Protection Measures.

Spending time in the sun increases your risk of skin cancer and early skin aging.
To decrease this risk, regularly use a sunscreen with a Broad Spectrum SPF value of 15 or higher and other sun protection measures including:

- Limit time in the sun, especially from 10 a.m.-2 p.m.
- Wear long-sleeved shirts, pants, hats, and sunglasses.

Inactive ingredients

Water, Propylheptyl Caprylate, Butyloctyl Salicylate, Propanediol, Caprylyl Methicone, Isododecane, Polyglyceryl-3 Polydimethylsiloxyethyl Dimethicone, Disteardimonium Hectorite, Polyglyceryl-2 Dipolyhydroxystearate, Polymethylsilsesquioxane, Magnesium Sulfate, Triethoxycaprylylsilane, Methyl Methacrylate Crosspolymer, 1,2-Hexanediol, Lauryl Polyglyceryl-3 Polydimethylsiloxyethyl Dimethicone, Glyceryl Caprylate, Caprylyl Glycol, Octyldodecanol, Ethylhexylglycerin, Echium Plantagineum Seed Oil, Tocopherol, Helianthus Annuus (Sunflower) Seed Oil Unsaponifiables, Sodium Hyaluronate, Panthenol, Cardiospermum Halicacabum Flower/Leaf/Vine Extract, Citric Acid

Other information

- Protect the product in this container from excessive heat and direct sun.

Dosage and Administration

Apply liberally 15 minutes before sun exposure.
Reapply at least every 2 hours.

Keep out of reach of children

WARNINGS

For external use only.

Do not use on damaged or broken skin.

When using this product, keep out of eyes. Rinse with water to remove.

Stop use and ask a doctor if rash occurs.

Keep out of reach of children.
If product is swallowed, get medical help or contact a Poison Control Center right away.

INDICATIONS AND USAGE

Helps prevent sunburn.

If used as directed with other sun protection measures (see Directions), decreases the risk of skin cancer and early skin aging caused by the sun.